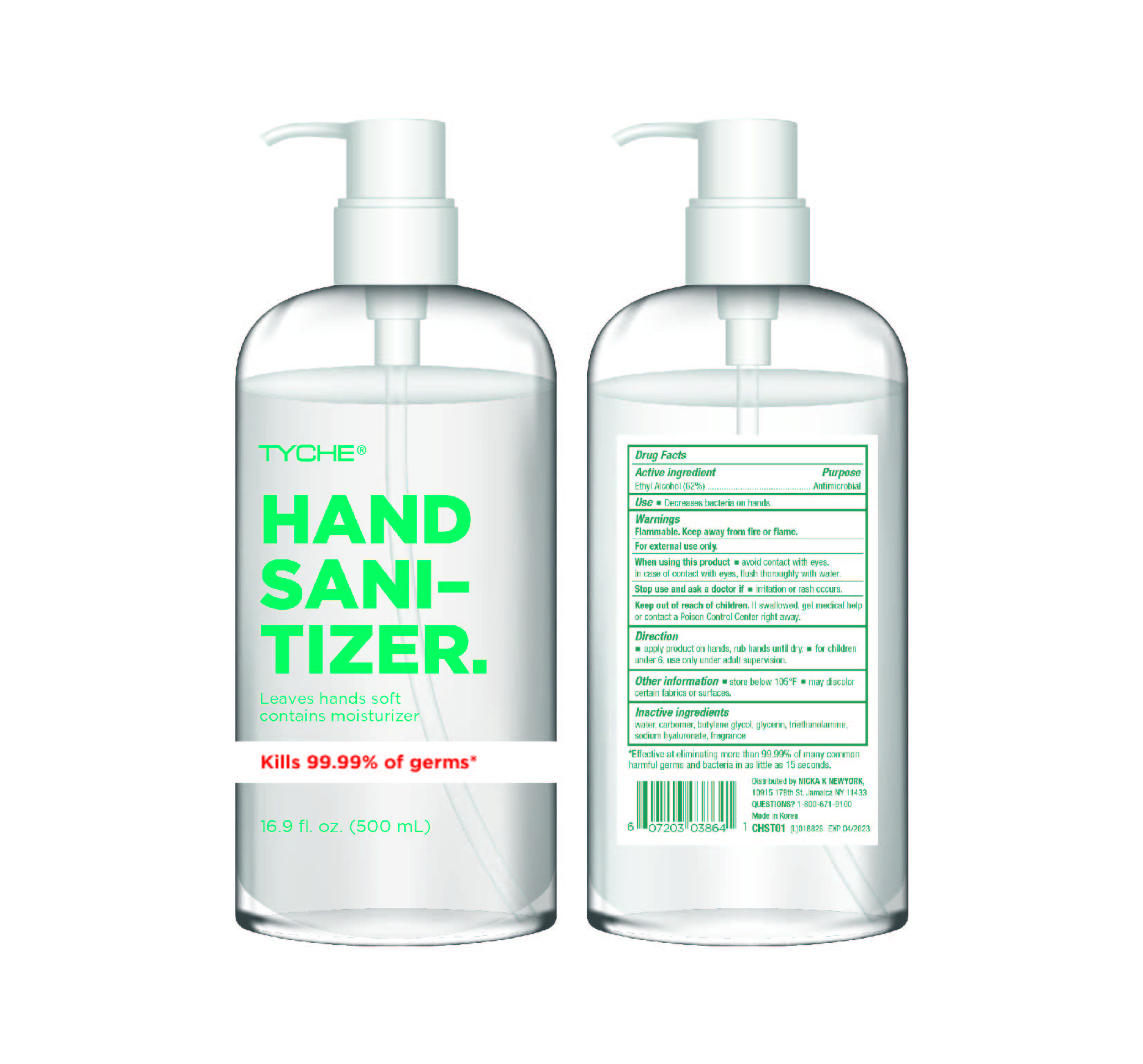 DRUG LABEL: TYCHE HAND SANITIZER
NDC: 74359-0562 | Form: GEL
Manufacturer: Proxima Inc.
Category: otc | Type: HUMAN OTC DRUG LABEL
Date: 20200403

ACTIVE INGREDIENTS: ALCOHOL 310 mL/500 mL
INACTIVE INGREDIENTS: GLYCERIN; CARBOMER HOMOPOLYMER, UNSPECIFIED TYPE; WATER; BUTYLENE GLYCOL; HYALURONATE SODIUM; TROLAMINE

[Proxima Inc.] 500 ml : 74359-0562